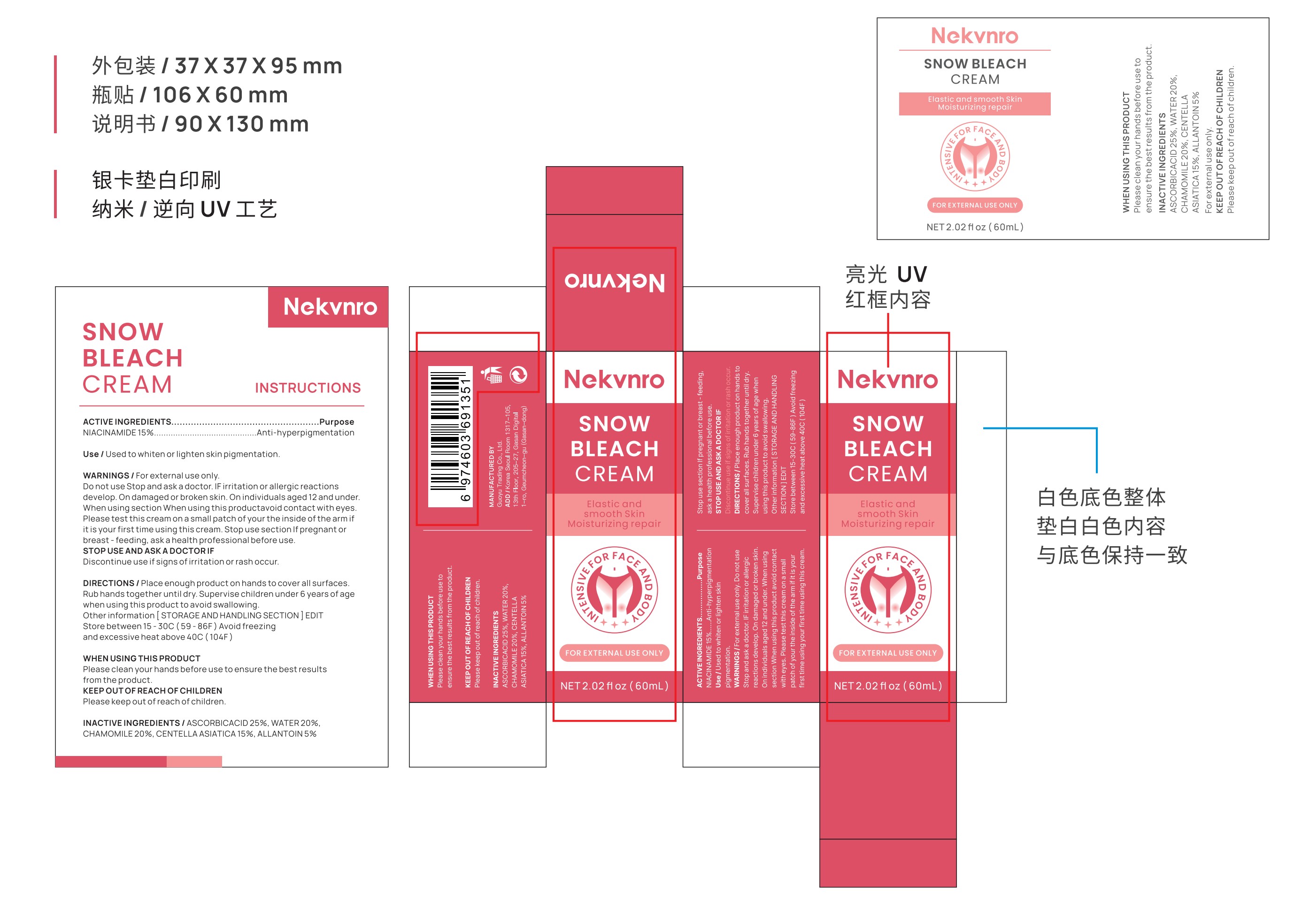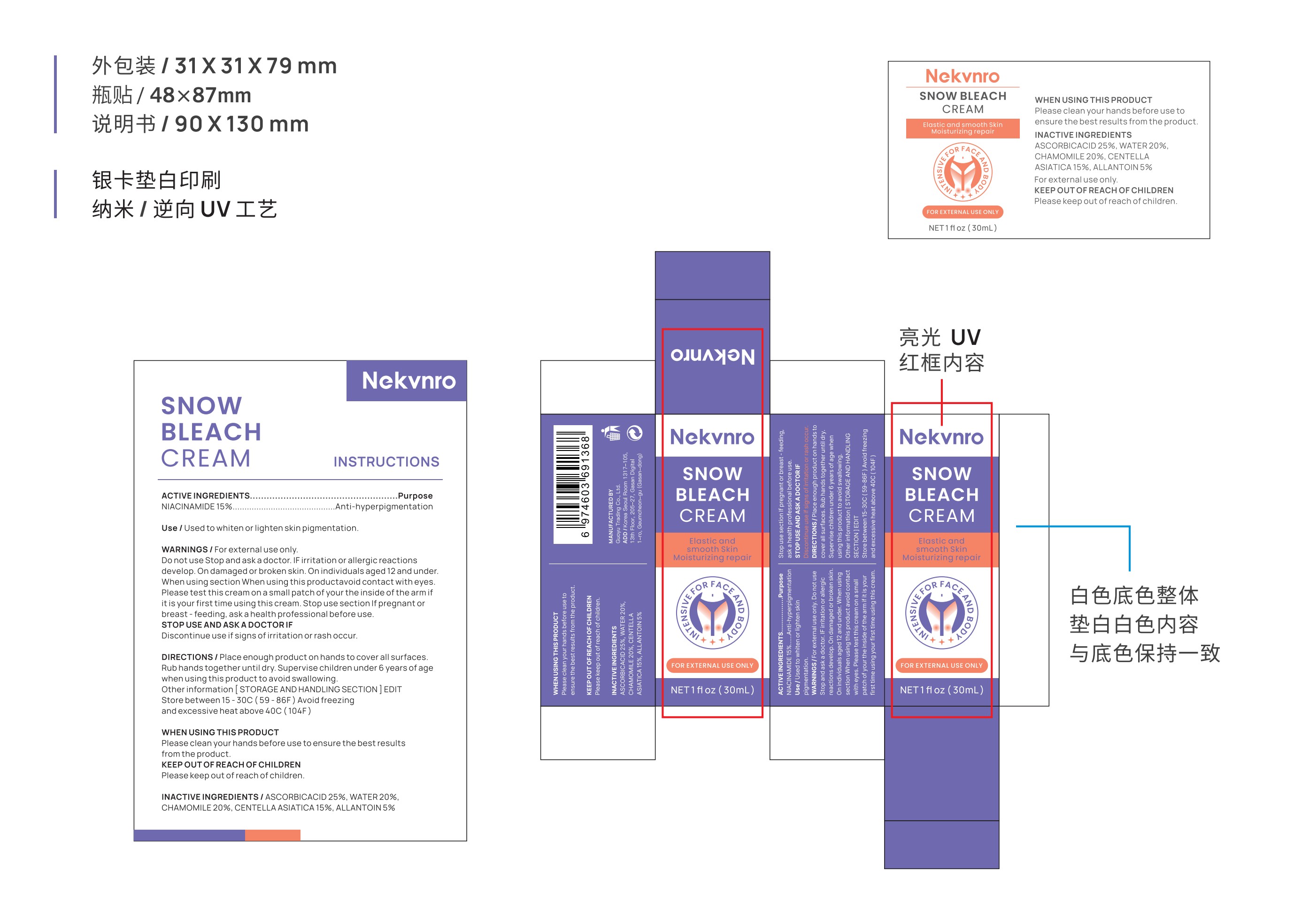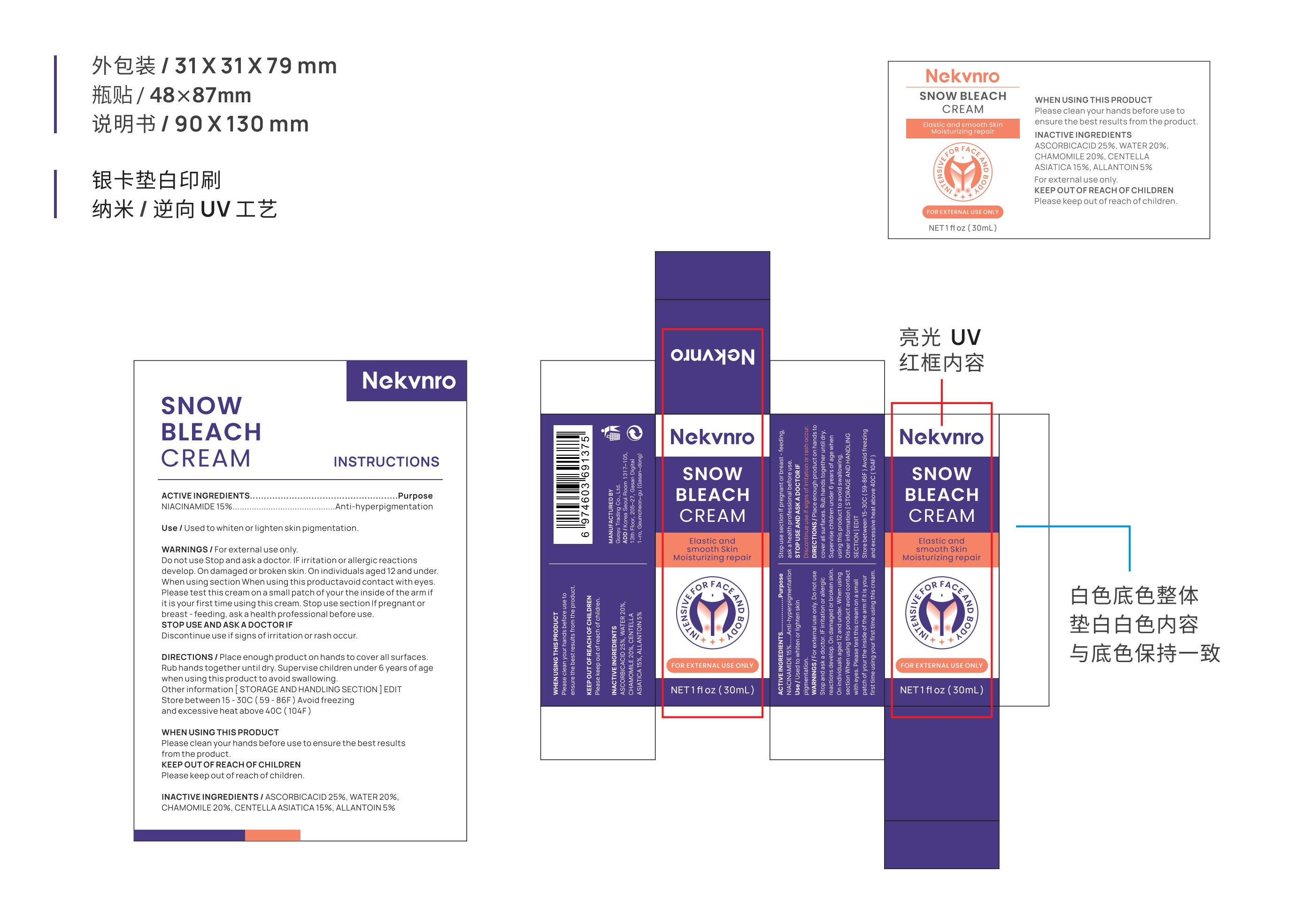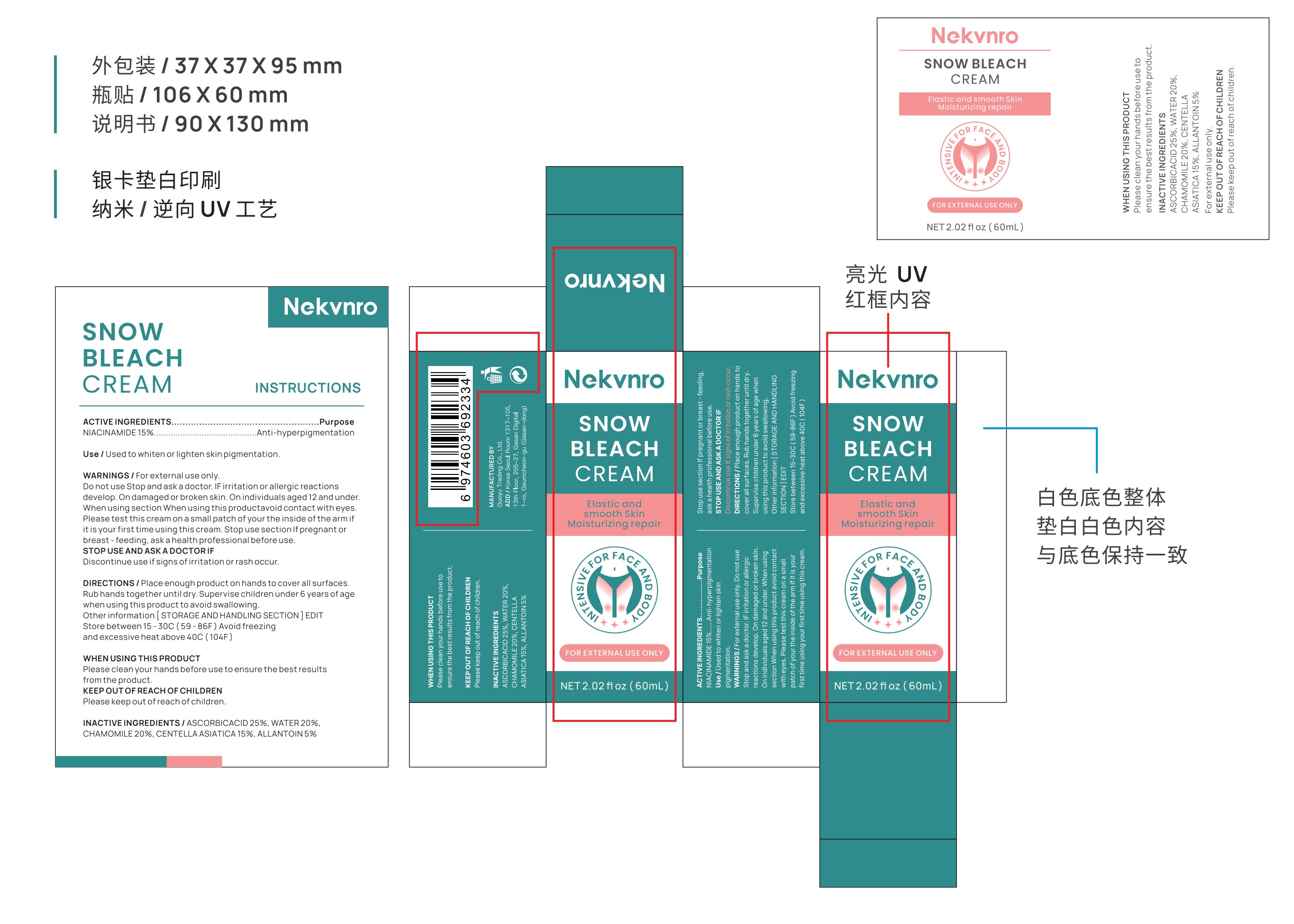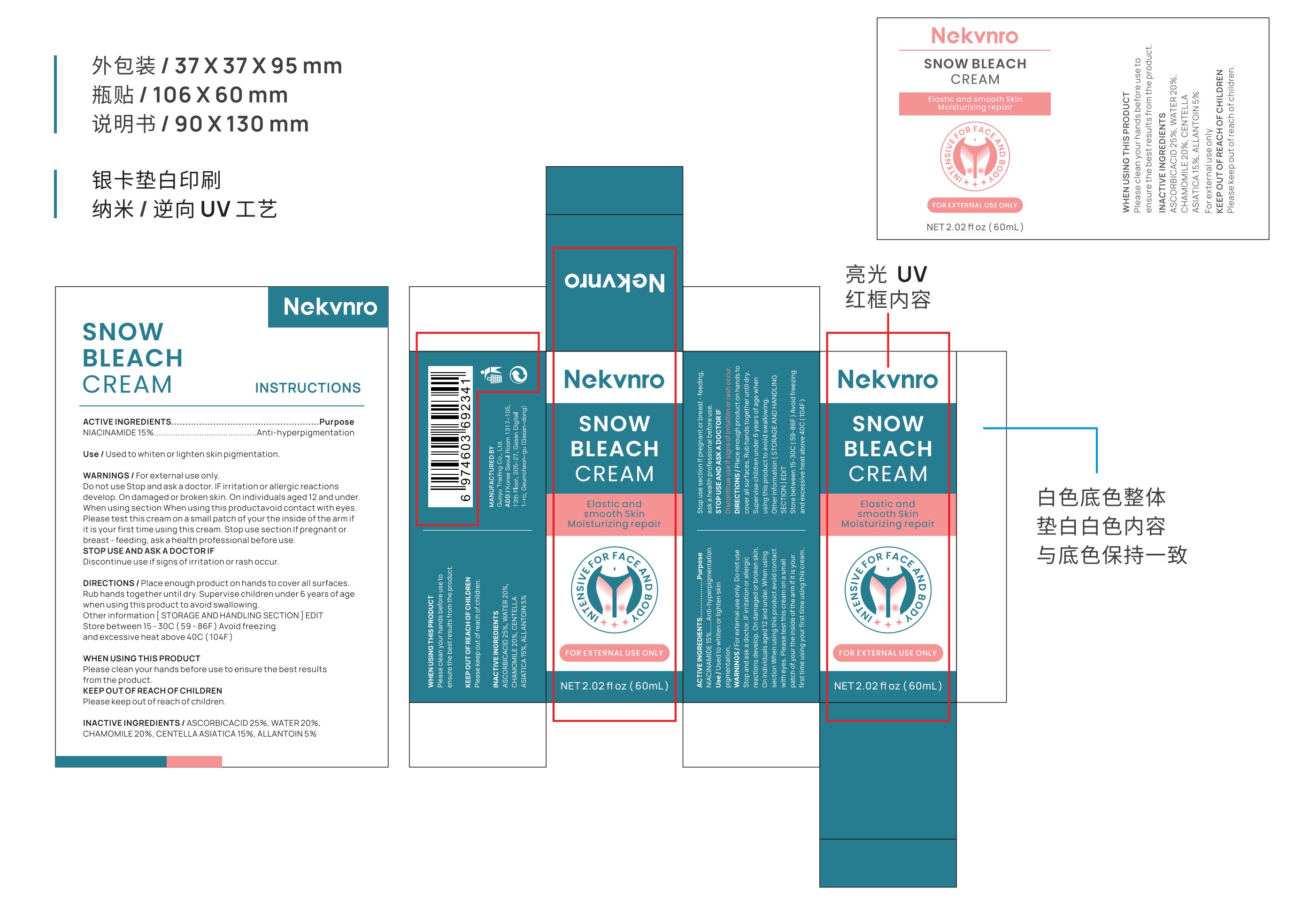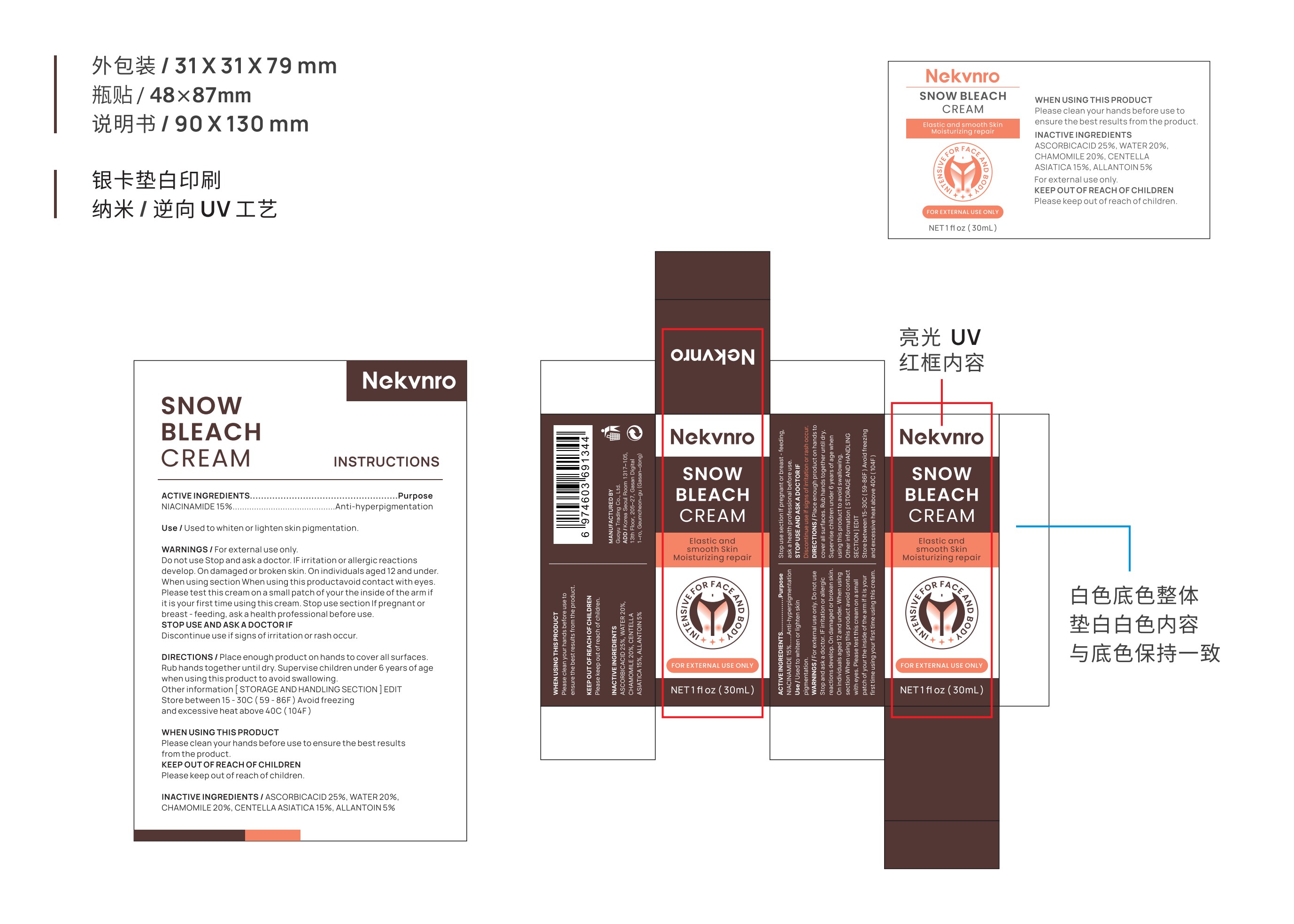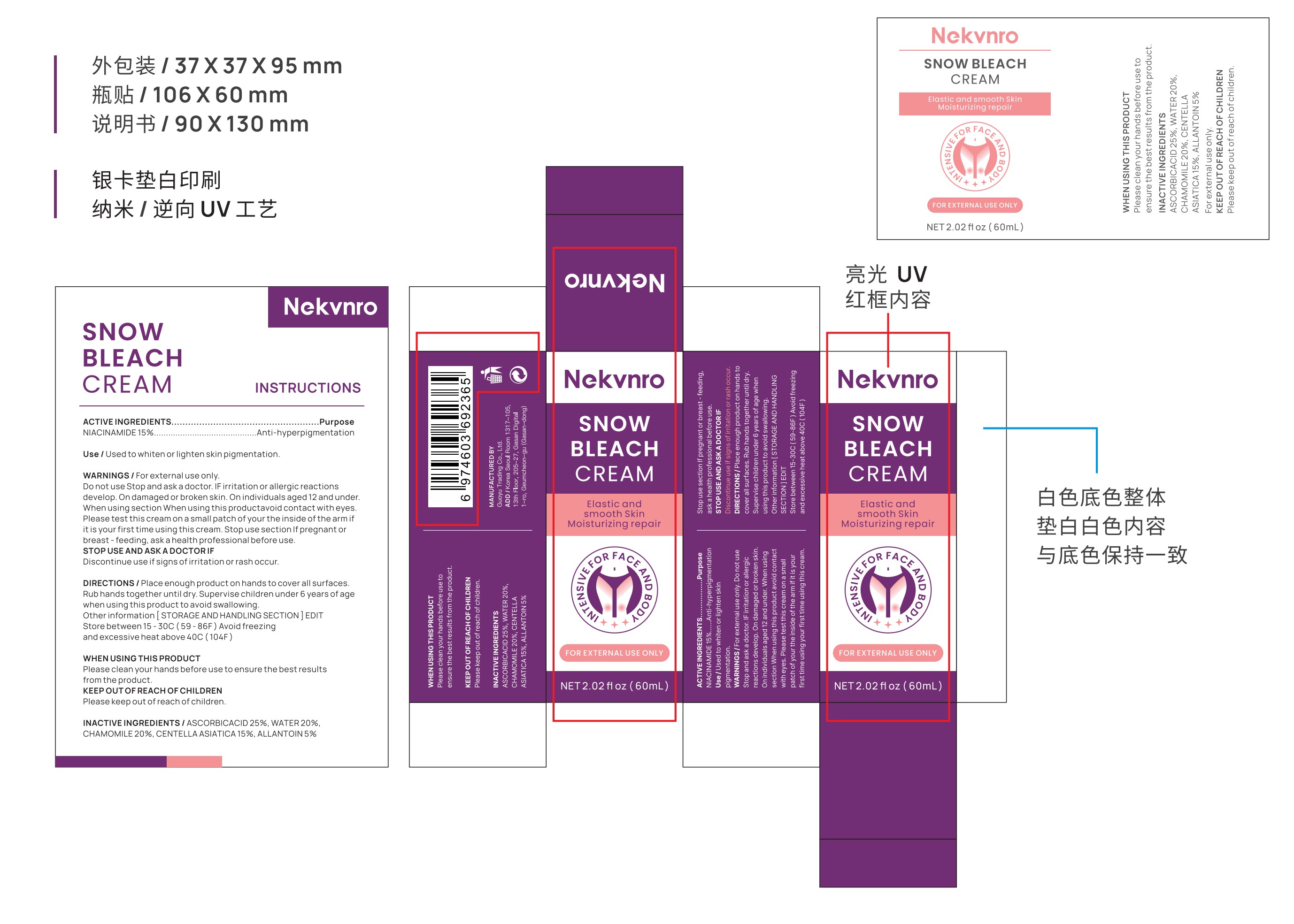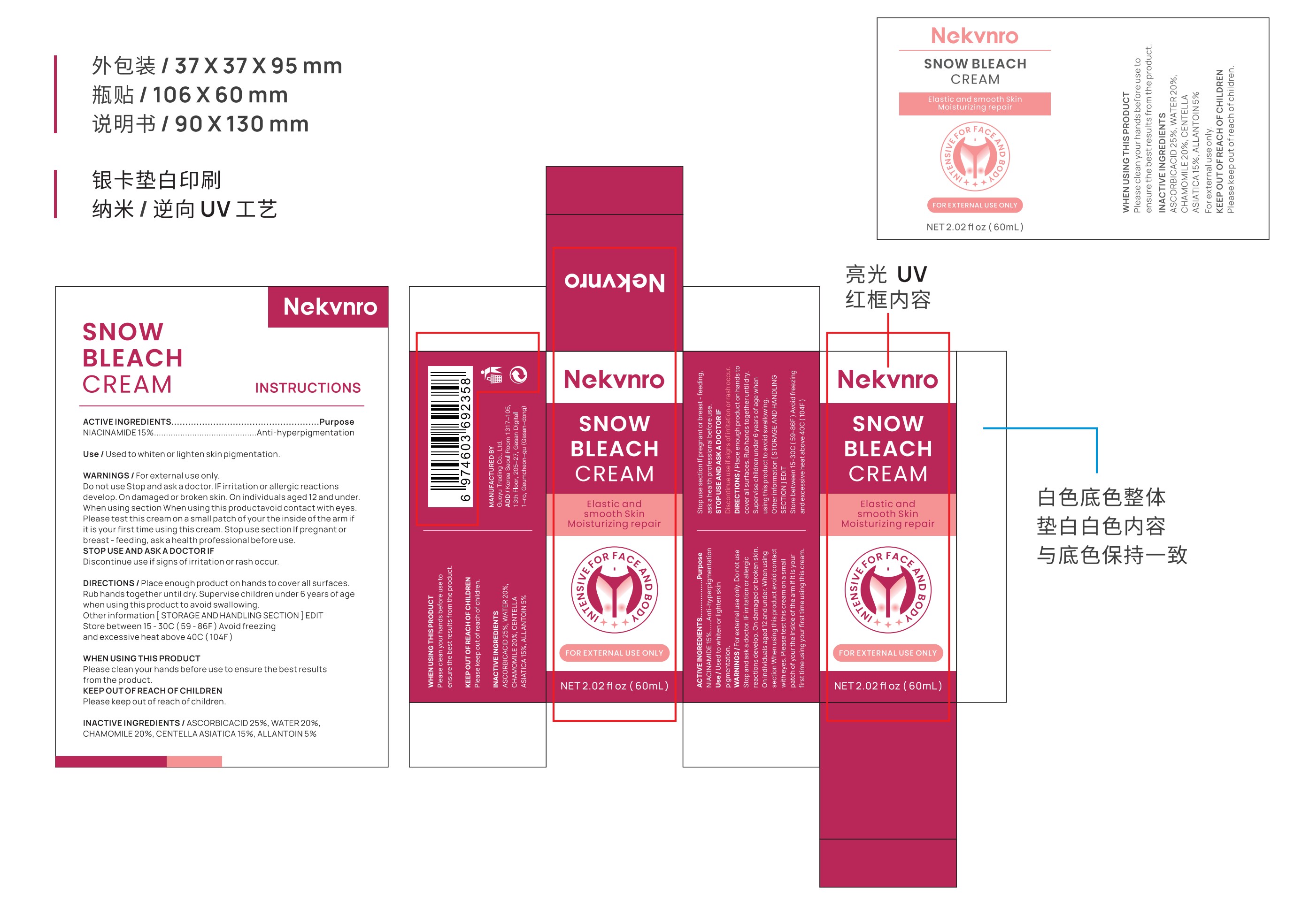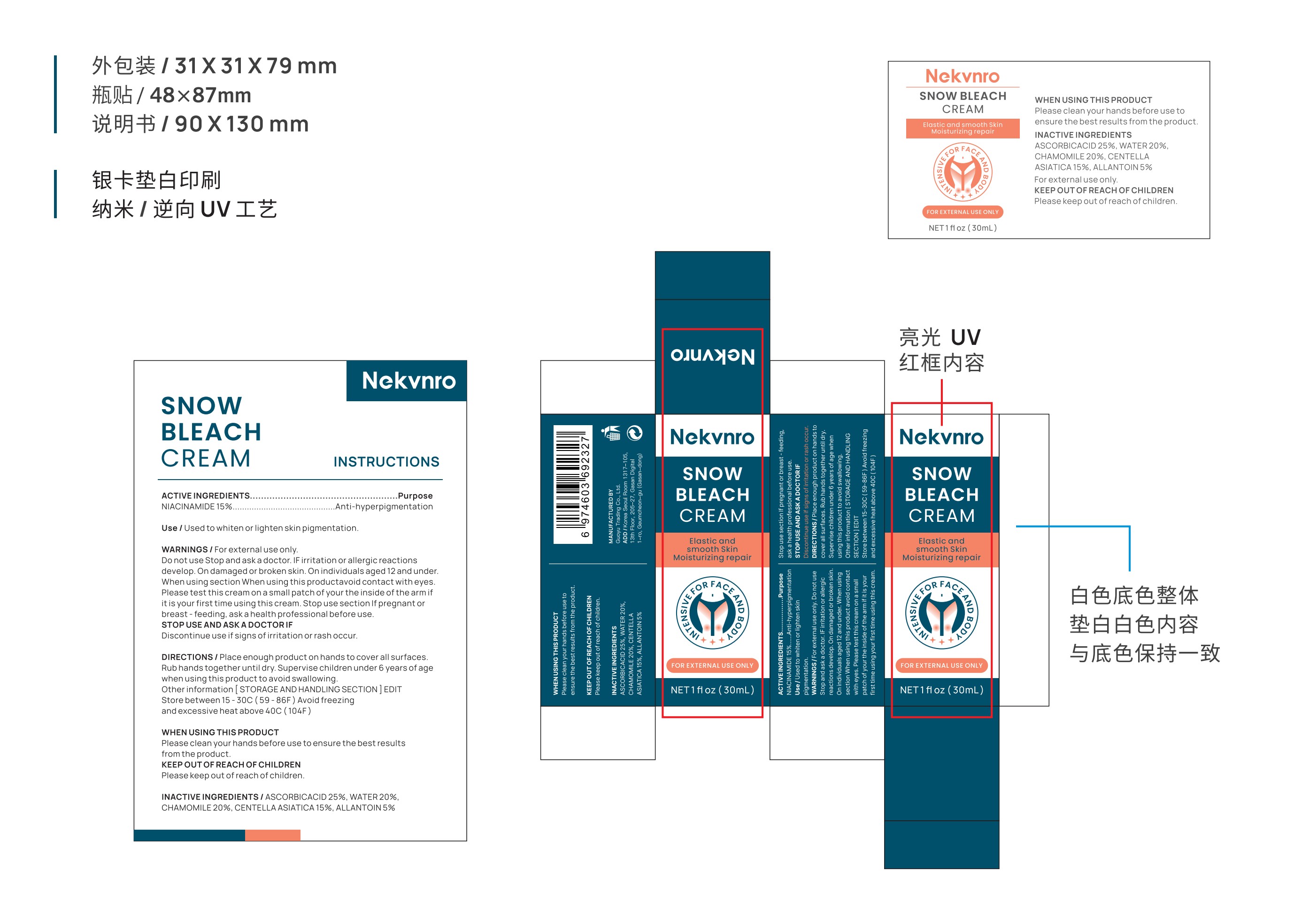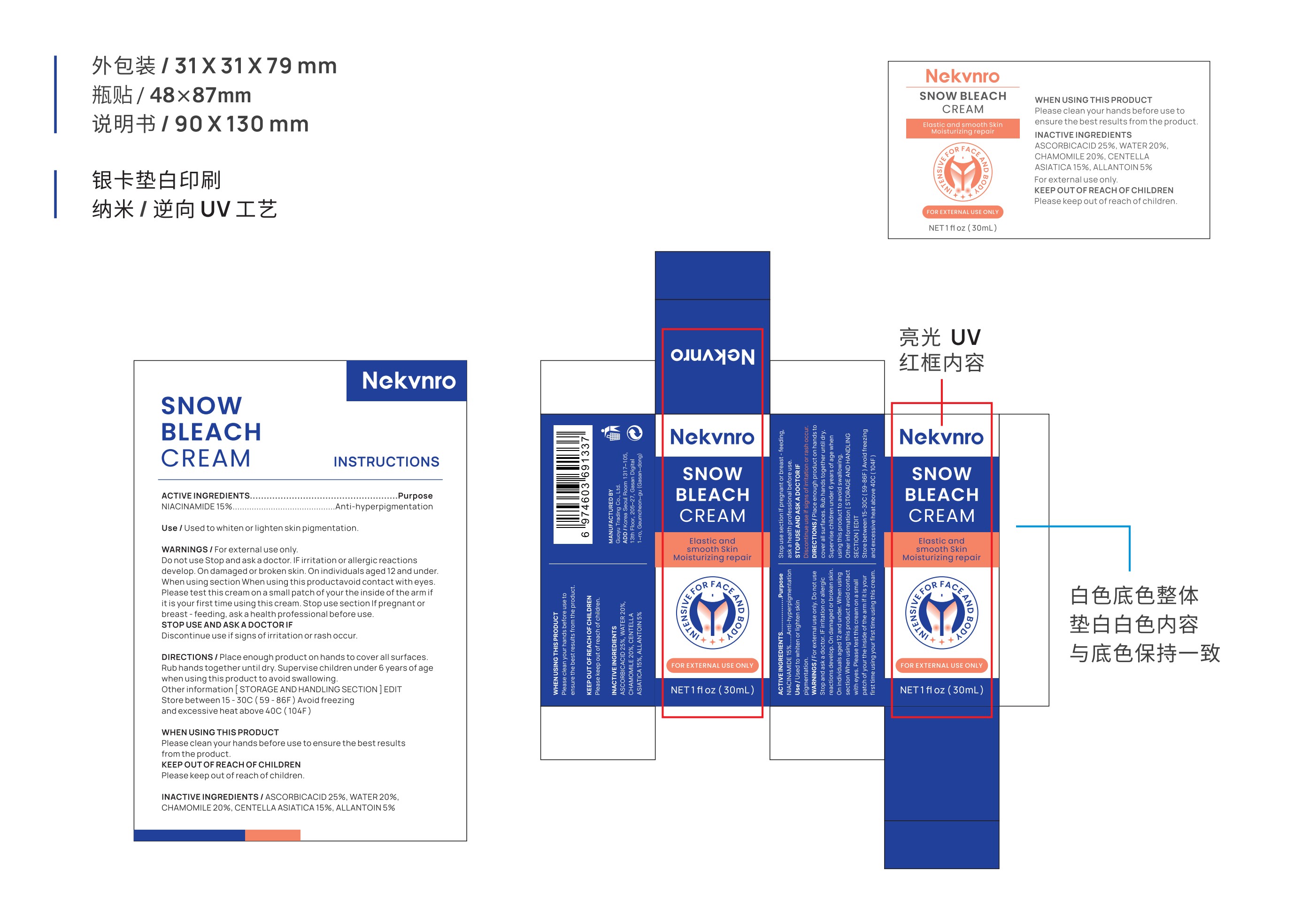 DRUG LABEL: Nekvnro Snow Bleach Cream
NDC: 84844-005 | Form: LIQUID
Manufacturer: Guoyu Trading Co., Ltd.
Category: otc | Type: HUMAN OTC DRUG LABEL
Date: 20241030

ACTIVE INGREDIENTS: NIACINAMIDE 15 g/100 mL
INACTIVE INGREDIENTS: ALLANTOIN; CENTELLA ASIATICA; WATER; CHAMOMILE; ASCORBIC ACID

84844-005

Active Ingredient

NIACINAMIDE 15%

Purpose

Anti-hyperpigmentation

Use

Used to whiten or lighten skin pigmentation.

Warnings

For external use only.

Do not use

if irritation or allergic reactions develop.
on damaged or broken skin. on individuals aged 12 and under.

When Using

section When using this productavoid contact with eyes.
Please test this cream on a small patch of your the inside of the arm if it is your first time using this cream.
Stop use section If pregnant or breast-feeding, ask a health professional before use.

Stop Use

Discontinue use if signs of irritation or rash occur.

Ask Doctor

Discontinue use if signs of irritation or rash occur.

Keep Oot Of Reach Of Children

Please keep out of reach of children.

Directions

Place enough product on hands to cover all surfaces.
Rub hands together until dry.
Supervise children under 6 years of age when using this product to avoid swallowing.

Other information

EDITStore between 15-30C (59-86F) Avoid freezingand excessive heat above 40C (104F)

Inactive ingredients

ASCORBIC ACID，WATER，CHAMOMILE，CENTELLA ASIATICA，ALLANTOIN